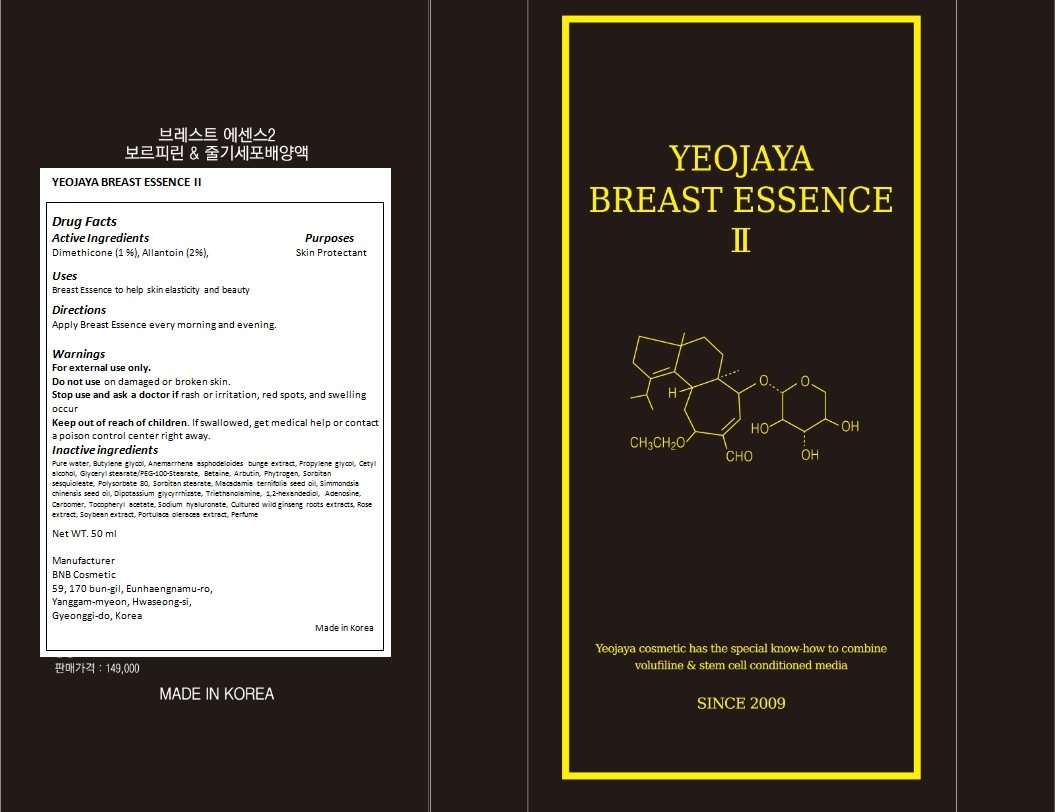 DRUG LABEL: Breast Essence II
NDC: 69142-001 | Form: CREAM
Manufacturer: yeojaya
Category: otc | Type: HUMAN OTC DRUG LABEL
Date: 20140729

ACTIVE INGREDIENTS: DIMETHICONE 0.5 mg/50 mL; ALLANTOIN 1 mg/50 mL
INACTIVE INGREDIENTS: WATER; BUTYLENE GLYCOL; ANEMARRHENA ASPHODELOIDES WHOLE; PROPYLENE GLYCOL; CETYL STEARATE; GLYCERYL MONOSTEARATE; BETAINE; ARBUTIN; SORBITAN SESQUIOLEATE; POLYSORBATE 80; SORBITAN MONOSTEARATE; MACADAMIA OIL; JOJOBA OIL; GLYCYRRHIZINATE DIPOTASSIUM; TROLAMINE; 1,2-HEXANEDIOL; Adenosine; CARBOMER HOMOPOLYMER TYPE C (ALLYL PENTAERYTHRITOL CROSSLINKED); .ALPHA.-TOCOPHEROL ACETATE; HYALURONATE SODIUM; ASIAN GINSENG; SOYBEAN SEED OIL; PURSLANE

Drug Facts

ACTIVE INGREDIENT

Dimethicone 1%

Allantoin 2%

PURPOSE

Skin Protectant

INDICATIONS AND USAGE

Breast Essence to help skin elasticity and beauty

WARNINGS

For external use only.

Do not use on damaged or broken skin.

Stop use and ask a doctor if rash or irritation, red spots, and swelling occur.

Keep out of reach of children.

When using this product, keep out of eyes.

INSTRUCTIONS FOR USE

Apply breast essence every morning and evening.

INACTIVE INGREDIENT

Pure water, Butylene glycol, Anemarrhena asphodeloides bunge extract, Propylene glycol, Cetyl alcohol, Glyceryl stearate/PEG-100-Stearate, Betaine, Arbutin, Phytrogen, Sorbitan sesquioleate, Polysorbate 80, Sorbitan stearate, Macadamia ternifolia seed oil, Simmondsia chinensis seed oil, Dipotassium glycyrrhizate, Triethanolamine, 1,2-hexandediol, Adenosine, Carbomer, Tocopheryl acetate, Sodium hyaluronate, Cultured wild ginseng roots extracts, Rose extract, Soybean extract, Portulaca oleracea extract, Perfume

DOSAGE AND ADMINISTRATION

Apply appropriate amount of essence every morning and evening.